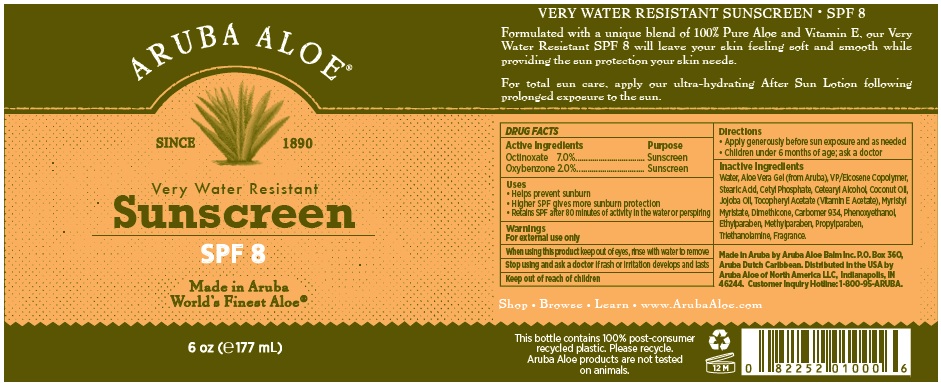 DRUG LABEL: Aruba Aloe Very Water Resistant Sunscreen
NDC: 53675-157 | Form: LOTION
Manufacturer: Aruba Aloe Balm, NV
Category: otc | Type: HUMAN OTC DRUG LABEL
Date: 20231114

ACTIVE INGREDIENTS: OXYBENZONE 20 mg/1 mL; OCTINOXATE 70 mg/1 mL
INACTIVE INGREDIENTS: WATER; ALOE VERA LEAF; STEARIC ACID; CETYL PHOSPHATE; CETOSTEARYL ALCOHOL; COCONUT OIL; JOJOBA OIL; ACETATE ION; MYRISTYL MYRISTATE; DIMETHICONE; CARBOMER 934; PHENOXYETHANOL; ETHYLPARABEN; METHYLPARABEN; PROPYLPARABEN; TROLAMINE

Aruba Aloe Very Water Resistant Sunscreen SPF 8

Active Ingredients

Octinoxate 7.0%
Oxybenzone 2.0%

Purpose

Sunscreen

Uses

- Helps prevent sunburn
- Higher SPF gives more sunburn protection
- Retains SPF after 80minutes of activity in the water

Warnings

For external use only/

When using this product

keep out of eyes, rinse with water to remove

Stop using and ask a doctor

if rash or irritation develops and lasts

Keep out of reach of children

Directions

Apply generously before sun exposure and as needed

Children under 6 months of age; ask a doctor

Inactive Ingredients

Water, Aruba Aloe Vera gel, VP/Eicosene Copolymer, stearic acid, cetyl phosphate, cetearyl alcohol, coconut oil, jojoba oil, tocopheryl acetate (Vitamin E Acetate), myristyl myristate, dimethicone, carbomer 934, phenoxyethanol, ethlparabven, methylparaben, propylparaben, triethanolamine, fragrance

Other Information

VERY WATER RESISTANT SUNSCREEN SPF 8

Formulated with a unique blend of 100% Pure Aloe and Vitamin E, our Very Water Resistant SPF 8 will leave your skin feeling soft and smooth while providing the sun protection your skin needs.

For total sun care, apply our ultra-hydrating After Sun Lotion following prolonged exposure to the skin.

Made in Aruba by Aruba Aloe Balm, Inc

PO Box 360, Aruba Dutch Caribbean. Distributed in the USA by Aruba Aloe of North America, LLC, Indianapolis, IN 46244. Customer inquiry Hotline: 1-800-95 ARUBA

Shop. Browse. Learn. www.ArubaAloe.com

Description

This bottle contains 100% post consumer recycled plastic. Please recycle. Aruba Aloe products are not tested on animals.

PACKAGE LABEL

ARUBA ALOE

since 1890

Very Water Resistant

Sunscreen SPF 8

Made in Aruba with the Worlds Finest Aloe (tm)